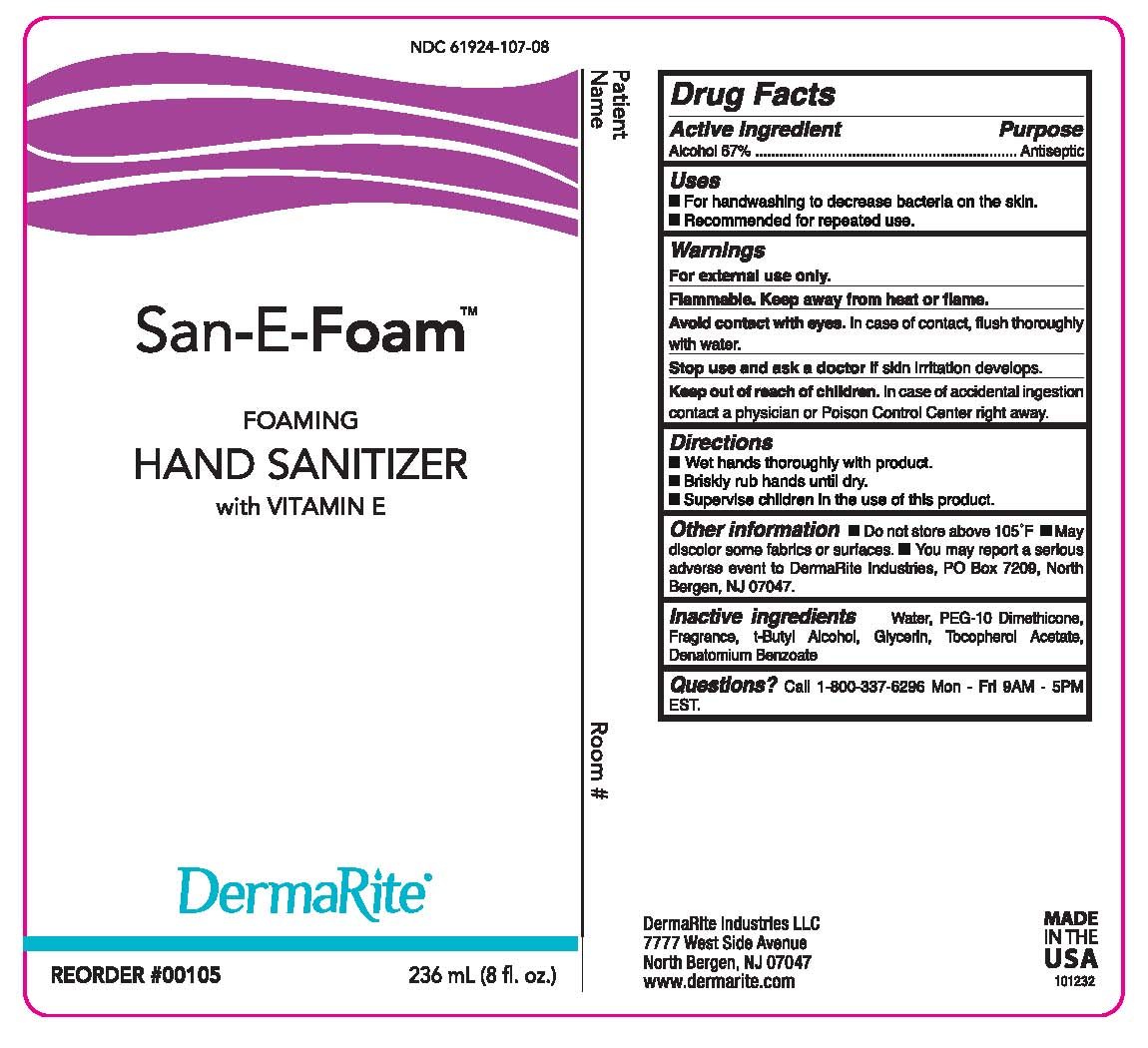 DRUG LABEL: SAN-E-FOAM
NDC: 61924-107 | Form: AEROSOL, FOAM
Manufacturer: Dermarite Industries LLC
Category: otc | Type: HUMAN OTC DRUG LABEL
Date: 20241205

ACTIVE INGREDIENTS: ALCOHOL 0.67 g/1 mL
INACTIVE INGREDIENTS: WATER; PEG-10 DIMETHICONE (600 CST); .ALPHA.-TOCOPHEROL ACETATE; GLYCERIN

DRUG LISTING: SAN-E-FOAM

Active Ingredient:

Ethyl Alcohol 67%

Purpose:

Antiseptic

Uses:

- For handwashing to decrease bacteria on the skin.
- Recommended for repeated use.

Warnings:

For external use only.

Flammable. Keep away from heat or flame.

Avoid contact with eyes. In case of contact, flush thoroughly with water.

Stop use and ask a doctor if skin irritation develops.

KEEP OUT OF REACH OF CHILDREN

In case of accidental ingestion contact a physician or Poison Control Center right away.

Directions

- Wet hands thoroughly with product.
- Briskly rub hands until dry.
- Supervise children in the use of this product.

Other Information

- Do not store above 105°F. May discolor some fabrics or surfaces.
- May report serious adverse events to DermaRite Industries, PO Box 7209, North Bergen, NJ 07047